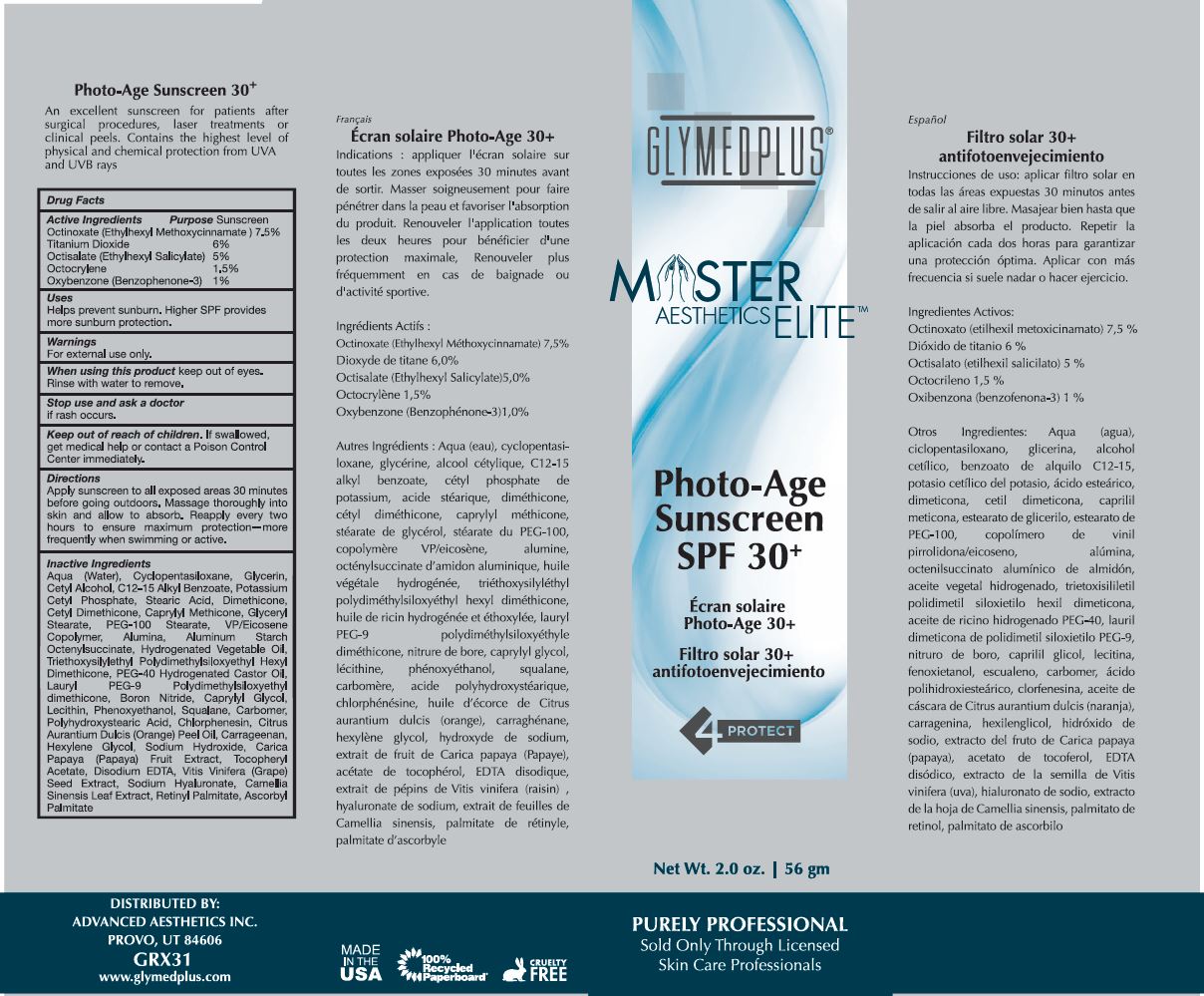 DRUG LABEL: PHOTO-AGE SUNSCREEN
NDC: 62551-213 | Form: GEL
Manufacturer: ADVANCED AESTHETICS
Category: otc | Type: HUMAN OTC DRUG LABEL
Date: 20230112

ACTIVE INGREDIENTS: OCTINOXATE 7.5 g/100 mL; OCTISALATE 5 g/100 mL; OCTOCRYLENE 1.5 g/100 mL; TITANIUM DIOXIDE 6 g/100 mL; OXYBENZONE 1 g/100 mL
INACTIVE INGREDIENTS: WATER; CYCLOMETHICONE 5; GLYCERIN; CETYL ALCOHOL; HYDROGENATED CASTOR OIL; TRIETHOXYSILYLETHYL POLYDIMETHYLSILOXYETHYL HEXYL DIMETHICONE; POLYOXYL 40 HYDROGENATED CASTOR OIL; LAURYL PEG-9 POLYDIMETHYLSILOXYETHYL DIMETHICONE; BORON NITRIDE; CAPRYLYL GLYCOL; LECITHIN, SOYBEAN; PHENOXYETHANOL; SQUALANE; CARBOMER HOMOPOLYMER, UNSPECIFIED TYPE; POLYHYDROXYSTEARIC ACID (2300 MW); CHLORPHENESIN; ORANGE OIL; CARRAGEENAN; HEXYLENE GLYCOL; SODIUM HYDROXIDE; PAPAYA; .ALPHA.-TOCOPHEROL ACETATE; EDETATE DISODIUM; VITIS VINIFERA SEED; HYALURONATE SODIUM; GREEN TEA LEAF; VITAMIN A PALMITATE; ASCORBYL PALMITATE; ALKYL (C12-15) BENZOATE; POTASSIUM CETYL PHOSPHATE; STEARIC ACID; DIMETHICONE; CETYL DIMETHICONE 25; CAPRYLYL TRISILOXANE; GLYCERYL MONOSTEARATE; PEG-100 STEARATE; EICOSYL POVIDONE; ALUMINUM OXIDE; ALUMINUM STARCH OCTENYLSUCCINATE

ADV AESTHETICS - GLYMEDPLUS MASTER AESTHETICS ELITE PHOTO-AGE SUNSCREEN SPF 30+ (62551-213)

ACTIVE INGREDIENTS

OCTINOXATE (ETHYLHEXYL METHOXYCINNAMATE) 7.5%

TITANIUM DIOXIDE 6%

OCTISALATE (ETHYLHEXYL SALICYLATE) 5%

OCTOCRYLENE 1.5%

OXYBENZONE (BENZOPHENONE-3) 1%

PURPOSE

SUNSCREEN

USES

HELPS PREVENT SUNBURN. HIGHER SPF PROVIDES MORE SUNBURN PROTECTION.

WARNINGS

FOR EXTERNAL USE ONLY.

WHEN USING THIS PRODUCT KEEP OUT OF EYES. RINSE WITH WATER TO REMOVE.

STOP USE AND ASK A DOCTOR IF RASH OCCURS.

KEEP OUT OF REACH OF CHILDREN. IF SWALLOWED, GET MEDICAL HELP OR CONTACT A POISON CONTROL CENTER IMMEDIATELY.

DIRECTIONS

APPLY SUNSCREEN TO ALL EXPOSED AREAS 30 MINUTES BEFORE GOING OUTDOORS. MASSAGE THOROUGHLY INTO SKIN AND ALLOW TO ABSORB. REAPPLY EVERY TWO HOURS TO ENSURE MAXIMUM PROTECTION - MORE FREQUENTLY WHEN SWIMMING OR ACTIVE.

INACTIVE INGREDIENTS

AQUA (WATER), CYCLOPENTASILOXANE, GLYCERIN, CETYL ALCOHOL, C12-15 ALKYL BENZOATE, POTASSIUM CETYL PHOSPHATE, STEARIC ACID, DIMETHICONE, CETYL DIMETHICONE, CAPRYLYL METHICONE, GLYCERYL STEARATE, PEG-100 STEARATE, VP/EICOSENE COPOLYMER, ALUMINA, ALUMINUM STARCH OCTENYLSUCCINATE, HYDROGENATED VEGETABLE OIL, TRIETHOXYSILYLETHYL POLYDIMETHYLSILOXYETHYL HEXYL DIMETHICONE, PEG-40 HYDROGENATED CASTOR OIL, LAURYL PEG-9 POLYDIMETHYLSILOXYETHYL DIMETHICONE, BORON NITRIDE, CAPRYLYL GLYCOL, LECITHIN, PHENOXYETHANOL, SQUALANE, CARBOMER, POLYHYDROXYSTEARIC ACID, CHLORPHENESIN, CITRUS AURANTIUM DULCIS (ORANGE) PEEL OIL, CARRAGEENAN, HEXYLENE GLYCOL, SODIUM HYDROXIDE, CARICA PAPAYA (PAPAYA) FRUIT EXTRACT, TOCOPHERYL ACETATE, DISODIUM EDTA, VITIS VINIFERA (GRAPE) SEED EXTRACT, SODIUM HYALURONATE, CAMELLIA SINENSIS LEAF EXTRACT, RETINYL PALMITATE, ASCORBYL PALMITATE.